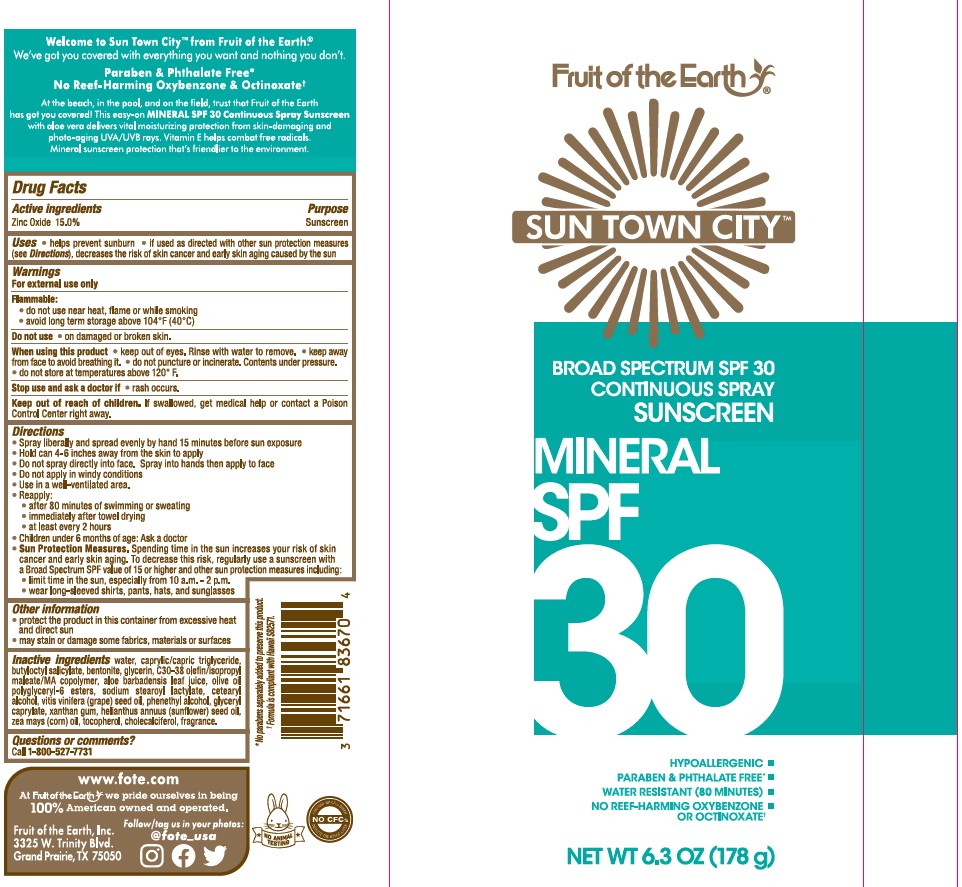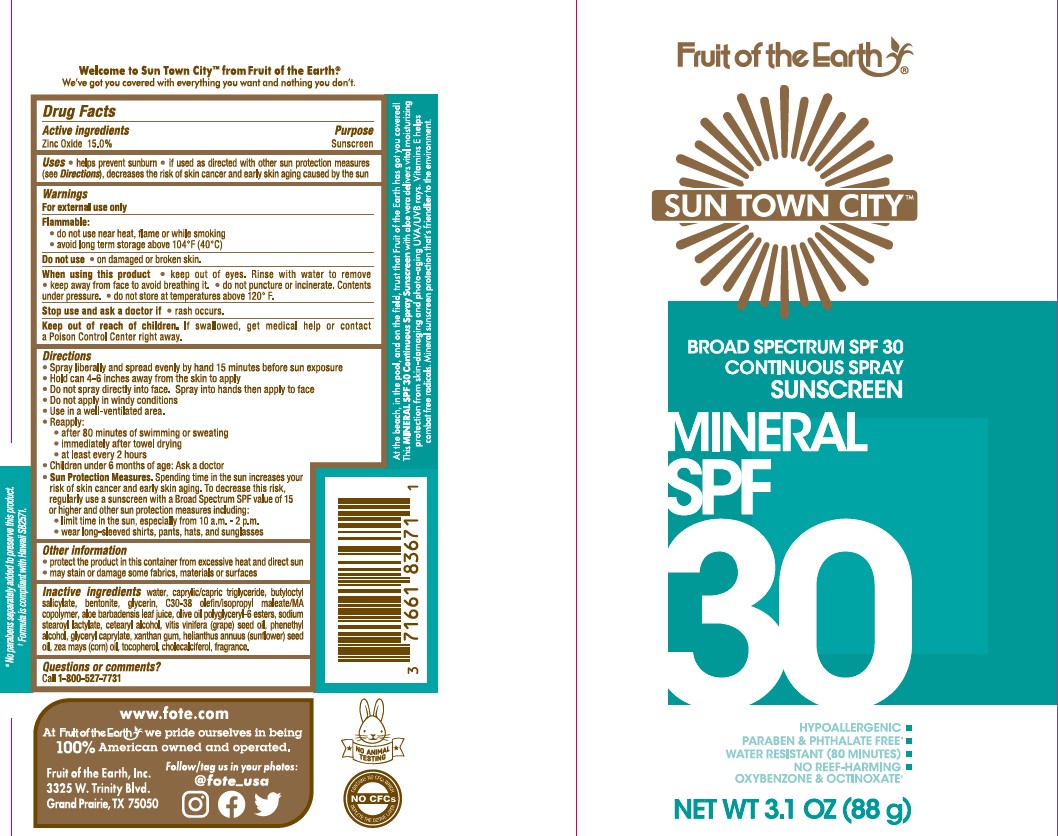 DRUG LABEL: Fruit of the Earth Sun Town City Mineral SPF 30 Sunscreen
NDC: 62217-244 | Form: SPRAY
Manufacturer: Fruit Of The Earth, Inc.
Category: otc | Type: HUMAN OTC DRUG LABEL
Date: 20241018

ACTIVE INGREDIENTS: ZINC OXIDE 150 mg/1 g
INACTIVE INGREDIENTS: GRAPE SEED OIL; OLIVE OIL POLYGLYCERYL-6 ESTERS; SUNFLOWER OIL; PHENYLETHYL ALCOHOL; BENTONITE; SODIUM STEAROYL LACTYLATE; CHOLECALCIFEROL; CORN OIL; GLYCERYL CAPRYLATE; WATER; CETYL ALCOHOL; MEDIUM-CHAIN TRIGLYCERIDES; .ALPHA.-TOCOPHEROL, DL-; ALOE VERA LEAF; GLYCERIN; XANTHAN GUM; BUTYLOCTYL SALICYLATE

Fruit of the Earth Sun Town City Mineral SPF 30 Sunscreen Spray

Active ingredients

Zinc Oxide 15.0%

Purpose

Sunscreen

Uses

- helps prevent sunburn
- if used as directed with other sun protection measures (see Directions), decreases the risk of skin cancer and early skin aging caused by the sun

Warnings

For external use only

FLAMMABLE:

• do not use near heat, flame or while smoking
• avoid long term storage above 104°F (40°C)

Do not use

- on damaged or broken skin

When using this product

• keep out of eyes. Rinse with water to remove.

• keep away from to avoid breathing it.

• do not puncture or incinerate. Contents under pressure.

• do not store at temperatures above 120° F.

Stop use and ask doctor if

- rash occurs.

Keep out of reach of children.

If product is swallowed, get medical help or contact a Poison Control Center right away.

Directions

• spray liberally and spread evenly by hand 15 minutes before sun exposure
• hold can 4-6 inches away from skin top apply
• do not spray into face. Spray into hand and apply to face.
• use in a well ventilated areas
reapply:
• after 80 minutes of swimming or sweating
• immediately after towel drying
• at least every 2 hours

• children under 6 months: Ask a doctor
• Sun Protection Measures. Spending time in the sun increases your risk of skin cancer and early skin aging. To decrease this risk, regularly use a sunscreen with a Broad Spectrum SPF Value of 15 or higher and other sun protection measures including:
• limit time in the sun, especially from 10 a.m. - 2 p.m.
• wear long-sleeved shirts, pants, hats, and sunglasses

Other Information

• protect the product in the container from excessive heat and direct sun
• may stain or damage some fabrics

Inactive ingredients

Water, Caprylic/Capric Triglyceride, Butyloctyl Salicylate, Bentonite, Glycerin, C30-38 Olefin/Isopropyl Maleate/MA Copolymer, Aloe Barbadensis Leaf Juice, Olive Oil Polyglyceryl-6 Esters, Sodium Stearoyl Lactylate, Cetearyl Alcohol, Vitis Vinifera (Grape) Seed Oil, Phenethyl Alcohol, Glyceryl Caprylate, Xanthan Gum, Helianthus Annuus (Sunflower) Seed Oil, Zay Mays (Corn) Oil, Tocopherol, Cholecalciferol, Fragrance